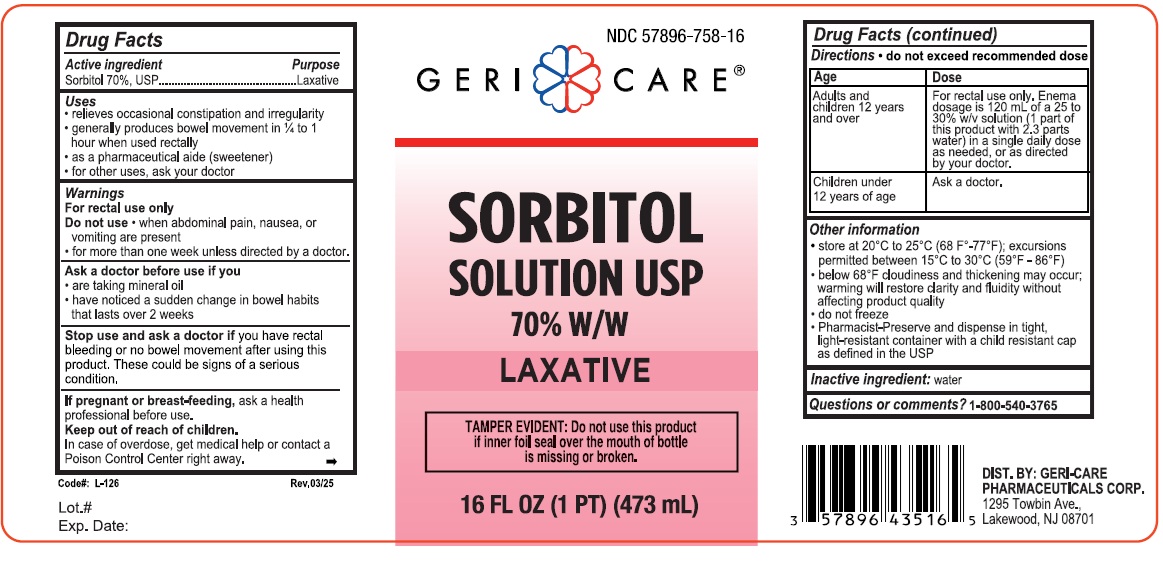 DRUG LABEL: GeriCare Sorbitol Solution
NDC: 57896-758 | Form: LIQUID
Manufacturer: GERI-CARE PHARMACEUTICALS, CORP
Category: otc | Type: HUMAN OTC DRUG LABEL
Date: 20251231

ACTIVE INGREDIENTS: SORBITOL 70 mg/100 mL
INACTIVE INGREDIENTS: WATER

GeriCare- Sorbitol 758

Active Ingredient

Sorbitol 70% USP

Purpose

Laxative

Uses

- releieves occasional constipation and irregularity
- generally produces bowel movement in 1/4 to 1 hour when used rectally
- as a pharmaceutical aide (sweetner)
- for other uses, ask your doctor

Warnings

For rectal use only

Do not use

- when abdominal pain, nausea, or vomiting are present
- for more than one week unless directed by a doctor

Ask a doctor before use if

- are taking mineral oil
- have noticed a sudden change in bowel habits that lasts over 2 weeks

Stop use and aska doctor if you have a rectal bleeding or no bowel movement after using this product. These could be signs of a serious condition.

PREGNANCY OR BREAST FEEDING

If pregnant or breast feeding ask a health professional before use.

Keep out of reach of children. In case of overdose, get medical help or contact a Poison Control Center right away.

DOSAGE AND ADMINISTRATION

Directions Do not exceed recommended dose

AGE | DOSE
Adults and children 12 years and over | For rectal use only. Enema dosage is 120 mL of a 25 to 30% w/v solution (1 part of this product with 2.3 parts water) in a single daily dose as needed, or as directed by your doctor.
Children under 12 years of age | Ask a doctor

Inactive ingredients water

Questions or comments? 1-800-540-3765